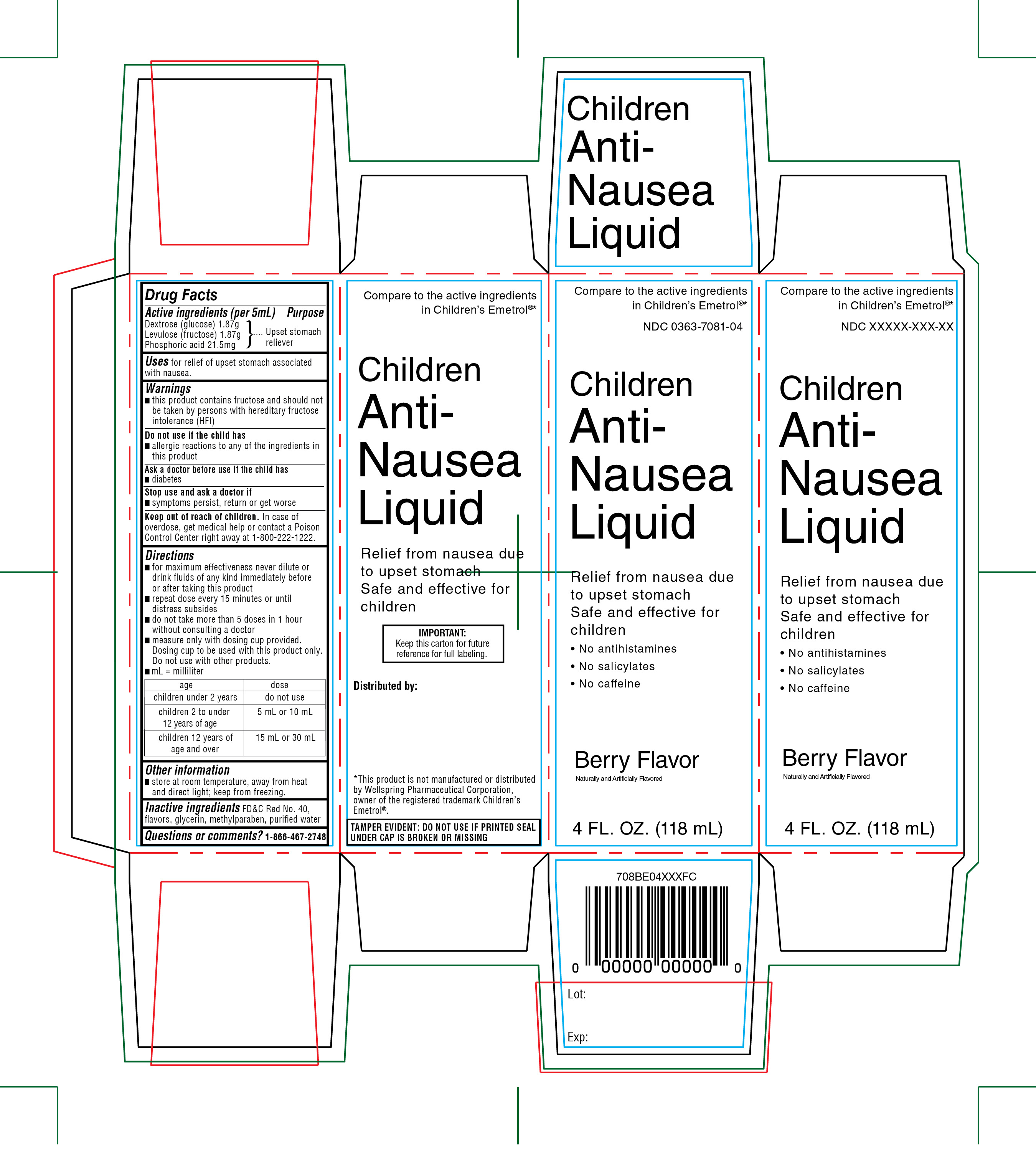 DRUG LABEL: WALGREEN
NDC: 0363-7081 | Form: SOLUTION
Manufacturer: WALGREENS CO.
Category: otc | Type: HUMAN OTC DRUG LABEL
Date: 20260116

ACTIVE INGREDIENTS: DEXTROSE, UNSPECIFIED FORM 1.87 g/5 mL; FRUCTOSE 1.87 g/5 mL; PHOSPHORIC ACID 21.5 mg/5 mL
INACTIVE INGREDIENTS: FD&C RED NO. 40; GLYCERIN; METHYLPARABEN; WATER

Walgreens Children Anti-Nausea Liquid

Active ingredients (per 5ml)

Dextrose (glucose)1.87 g

Levulose (fructose)1.87 g

Phosphoric acid 21.5 mg

Purpose

Upset Stomach Reliever

Uses

For relief of upset stomach associated with nausea

Warnings

- this product contains fructose and should not be taken by persons with hereditary fructose intolerance (HFI).

Do not use if the child has

- allergic reactions to any of the ingredients in this product

Ask a doctor before use if the child has

- diabetes

Stop use and ask a doctor if

- symptoms persist, return or get worse

Keep out of reach of children.

In case of overdose, get medical help or contact a Poison Control Center right away at 1-800-222-1222.

Directions

- for maximum effectiveness never dilute or drink fluids of any kind immediately before or after taking this product
- repeat dose every 15 minutes or until distress subsides
- do not take more than 5 doses in 1 hour without consulting a doctor
- measure only with dosing cup provided. Dosing cup to be used with this product only. Do not use with other products.
- mL= milliliter

age | dose
children under 2 years | Do not use
children 2 to under 12 years of age | 5 mL or 10mL
children 12 years of age and over | 15 mL or 30 mL

Other information

- Store at room temperature, away from heat and direct light; keep from freezing

Inactive ingredients

FD&C red no. 40, flavors, glycerin, methylparaben, and purified water.

Questions or Comments?

1-866-467-2748

PACKAGE LABEL

Compare to the active ingredients in Children’s Emetrol®*

NDC 0363-7081-04

Children Anti-Nausea Liquid

Relief from nausea due to upset stomach

Safe and effective for children

- No antihistamines
- No salicylates
- No caffeine

Berry Flavor

Naturally and Artificially Flavored

4 FL. OZ. (118 mL)

IMPORTANT: Keep this carton for future reference for full labeling.

TAMPER EVIDENT: DO NOT USE IF PRINTED SEAL UNDER CAP IS BROKEN OR MISSING

Distributed by

*This product is not manufactured or distributed by Wellspring Pharmaceutical Corporation, owner of the registered trademark Children’s Emetrol®.